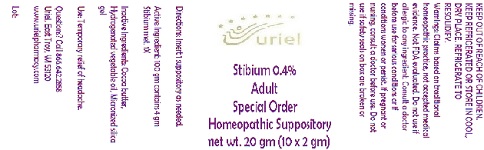 DRUG LABEL: Stibium 0.4 Adult Size Special Order
NDC: 48951-8292 | Form: SUPPOSITORY
Manufacturer: Uriel Pharmacy Inc.
Category: homeopathic | Type: HUMAN OTC DRUG LABEL
Date: 20180501

ACTIVE INGREDIENTS: ANTIMONY 3 [hp_X]/1 g
INACTIVE INGREDIENTS: COCOA BUTTER; CORN OIL; SILICON DIOXIDE

Stibium 0.4 Adult Size Special Order

INDICATIONS AND USAGE

Directions: FOR RECTAL USE ONLY.

DOSAGE AND ADMINISTRATION

Insert 1 suppository as needed.

Active Ingredient: 100 gm contains 4 gm Stibium met. 1X

INACTIVE INGREDIENT

Inactive Ingredients: Cocoa butter, Hydrogenated vegetable oil, Micronized silica gel

PURPOSE

Use: Temporary relief of headache.

KEEP OUT OF REACH OF CHILDREN.

WARNINGS

KEEP REFRIGERATED OR STORE IN COOL, DRY PLACE. REFRIGERATE TO RESOLIDIFY.
Warnings: Claims based on traditional homeopathic practice, not accepted medical evidence. Not FDA evaluated. Do not use if allergic to any ingredient. Consult a doctor before use for serious conditions or if conditions worsen or persist. If pregnant or nursing, consult a doctor before use. Do not use if safety seals on box are broken or missing.

QUESTIONS

Questions? Call 866.642.2858 Uriel, East Troy, WI 53120 www.urielpharmacy.com